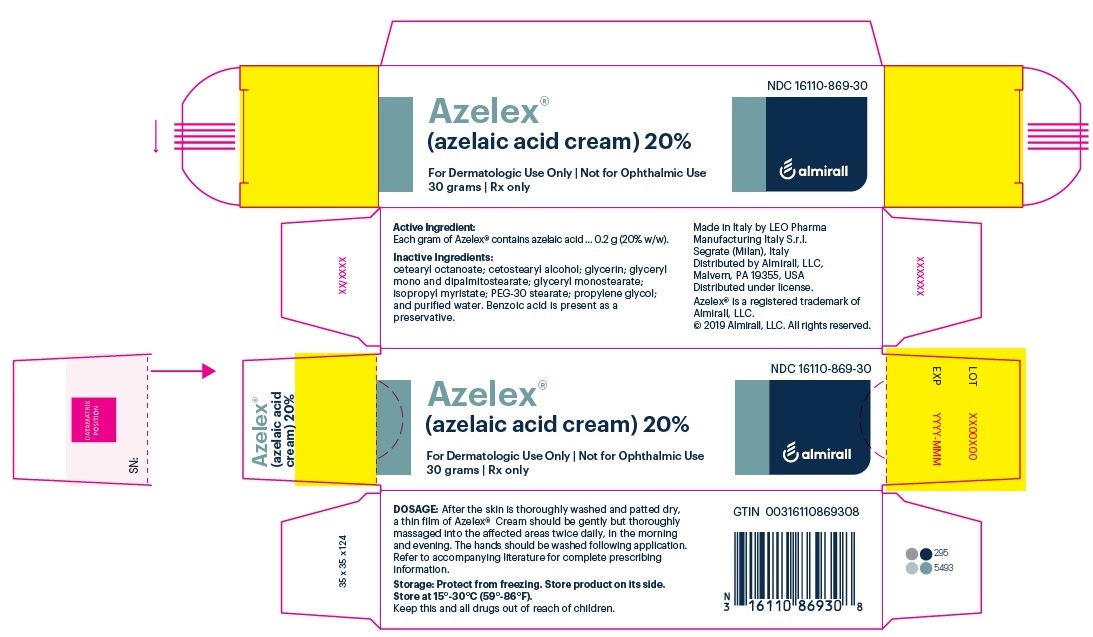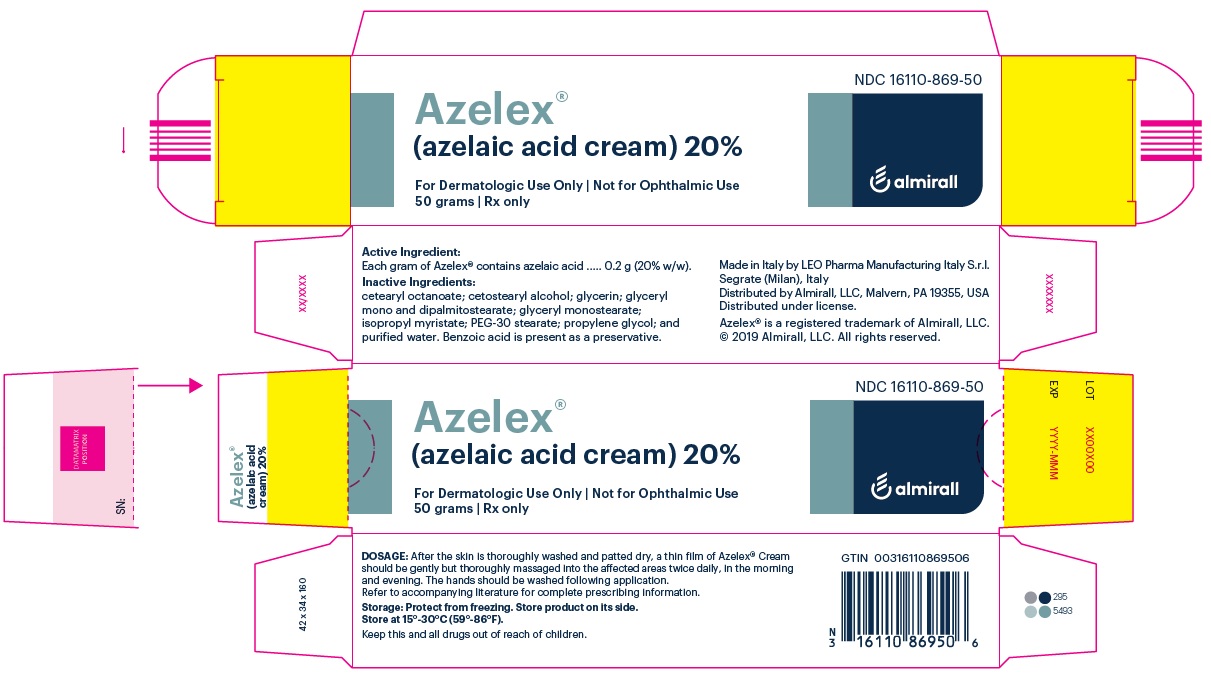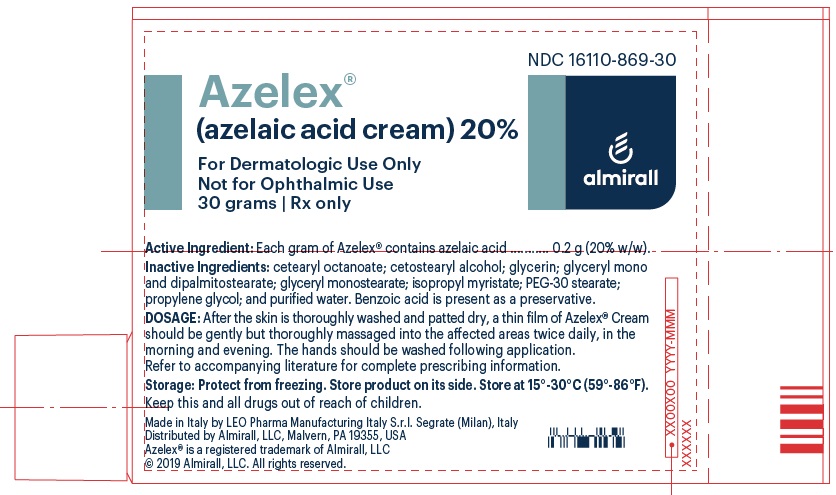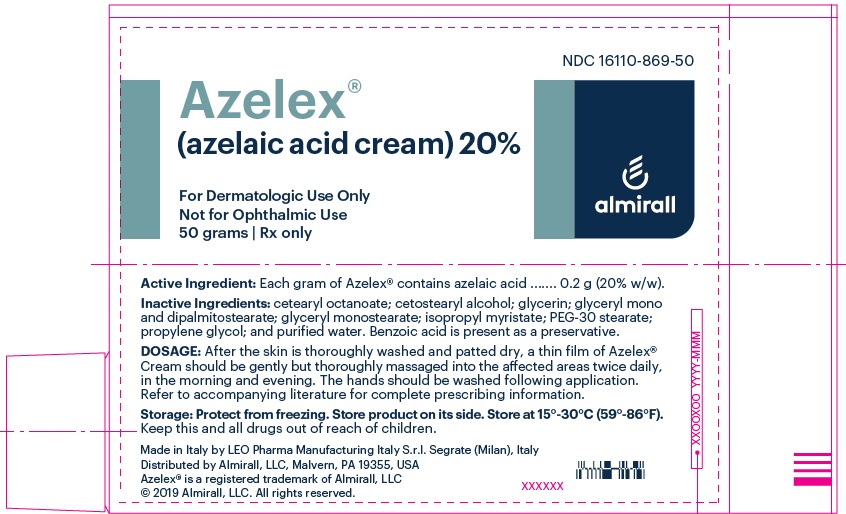 DRUG LABEL: AZELEX
NDC: 16110-869 | Form: CREAM
Manufacturer: Almirall, LLC
Category: prescription | Type: HUMAN PRESCRIPTION DRUG LABEL
Date: 20240304

ACTIVE INGREDIENTS: AZELAIC ACID 0.2 g/1 g
INACTIVE INGREDIENTS: CETEARYL ETHYLHEXANOATE; ISOPROPYL MYRISTATE ; GLYCERYL MONOSTEARATE; PEG-30 STEARATE; CETOSTEARYL ALCOHOL; GLYCERYL MONO AND DIPALMITOSTEARATE; GLYCERIN; PROPYLENE GLYCOL; WATER; BENZOIC ACID

AZELEX®
(azelaic acid cream) 20%

For Dermatologic Use Only
Not for Ophthalmic Use

DESCRIPTION

AZELEX® (azelaic acid cream) 20% contains azelaic acid, a naturally occurring saturated dicarboxylic acid.

Structural Formula: HOOC-(CH2)7-COOH

Chemical Name: 1,7-heptanedicarboxylic acid

Empirical Formula: C9H16O4

Molecular Weight: 188.22

Active Ingredient: Each gram of AZELEX® contains azelaic acid......... 0.2 g (20% w/w).

Inactive Ingredients: cetearyl octanoate; cetostearyl alcohol; glycerin; glyceryl mono and dipalmitostearate; glyceryl monostearate; isopropyl myristate; PEG-30 stearate; propylene glycol; and purified water. Benzoic acid is present as a preservative.

CLINICAL PHARMACOLOGY

The exact mechanism of action of azelaic acid is not known. The following in vitro data are available, but their clinical significance is unknown. Azelaic acid has been shown to possess antimicrobial activity against Propionibacterium acnes and Staphylococcus epidermidis. The antimicrobial action may be attributable to inhibition of microbial cellular protein synthesis.

A normalization of keratinization leading to an anticomedonal effect of azelaic acid may also contribute to its clinical activity. Electron microscopic and immunohistochemical evaluation of skin biopsies from human subjects treated with AZELEX® cream demonstrated a reduction in the thickness of the stratum corneum, a reduction in number and size of keratohyalin granules, and a reduction in the amount and distribution of filaggrin (a protein component of keratohyalin) in epidermal layers. This is suggestive of the ability to decrease microcomedo formation.

Pharmacokinetics

Following a single application of AZELEX® cream to human skin in vitro, azelaic acid penetrates into the stratum corneum (approximately 3 to 5% of the applied dose) and other viable skin layers (up to 10% of the dose is found in the epidermis and dermis). Negligible cutaneous metabolism occurs after topical application. Approximately 4% of the topically applied azelaic acid is systemically absorbed. Azelaic acid is mainly excreted unchanged in the urine but undergoes some β-oxidation to shorter chain dicarboxylic acids. The observed half-lives in healthy subjects are approximately 45 minutes after oral dosing and 12 hours after topical dosing, indicating percutaneous absorption rate-limited kinetics.

Azelaic acid is a dietary constituent (whole grain cereals and animal products), and can be formed endogenously from longer-chain dicarboxylic acids, metabolism of oleic acid, and ψ-oxidation of monocarboxylic acids. Endogenous plasma concentration (20 to 80 ng/mL) and daily urinary excretion (4 to 28 mg) of azelaic acid are highly dependent on dietary intake. After topical treatment with AZELEX® cream in humans, plasma concentration and urinary excretion of azelaic acid are not significantly different from baseline levels.

INDICATIONS AND USAGE

AZELEX® cream is indicated for the topical treatment of mild-to-moderate inflammatory acne vulgaris.

CONTRAINDICATIONS

AZELEX® cream is contraindicated in individuals who have shown hypersensitivity to any of its components.

WARNINGS

AZELEX® cream is for dermatologic use only and not for ophthalmic use.

There have been isolated reports of hypopigmentation after use of azelaic acid. Since azelaic acid has not been well studied in patients with dark complexions, these patients should be monitored for early signs of hypopigmentation.

PRECAUTIONS

General

If sensitivity or severe irritation develop with the use of AZELEX® cream, treatment should be discontinued and appropriate therapy instituted.

Information for Patients

Patients should be told:

1. To use AZELEX® cream for the full prescribed treatment period.
2. To avoid the use of occlusive dressings or wrappings.
3. To keep AZELEX® cream away from the mouth, eyes and other mucous membranes. If it does come in contact with the eyes, they should wash their eyes with large amounts of water and consult a physician if eye irritation persists.
4. If they have dark complexions, to report abnormal changes in skin color to their physician.
5. Due in part to the low pH of azelaic acid, temporary skin irritation (pruritus, burning, or stinging) may occur when AZELEX® cream is applied to broken or inflamed skin, usually at the start of treatment. However, this irritation commonly subsides if treatment is continued. If it continues, AZELEX

Carcinogenesis, Mutagenesis, Impairment of Fertility

Azelaic acid is a human dietary component of a simple molecular structure that does not suggest carcinogenic potential, and it does not belong to a class of drugs for which there is a concern about carcinogenicity. Therefore, animal studies to evaluate carcinogenic potential with AZELEX® cream were not deemed necessary. In a battery of tests (Ames assay, HGPRT test in Chinese hamster ovary cells, human lymphocyte test, dominant lethal assay in mice), azelaic acid was found to be nonmutagenic. Animal studies have shown no adverse effects on fertility.

Pregnancy

Teratogenic Effects

Embryotoxic effects were observed in Segment I and Segment II oral studies with rats receiving 2500 mg/kg/day of azelaic acid. Similar effects were observed in Segment II studies in rabbits given 150 to 500 mg/kg/day and in monkeys given 500 mg/kg/day. The doses at which these effects were noted were all within toxic dose ranges for the dams. No teratogenic effects were observed. There are, however, no adequate and well-controlled studies in pregnant women. Because animal reproduction studies are not always predictive of human response, this drug should be used during pregnancy only if clearly needed.

Nursing Mothers

Equilibrium dialysis was used to assess human milk partitioning in vitro. At an azelaic acid concentration of 25 mcg/mL, the milk/plasma distribution coefficient was 0.7 and the milk/buffer distribution was 1.0, indicating that passage of drug into maternal milk may occur. Since less than 4% of a topically applied dose is systemically absorbed, the uptake of azelaic acid into maternal milk is not expected to cause a significant change from baseline azelaic acid levels in the milk. However, caution should be exercised when AZELEX® cream is administered to a nursing mother.

Pediatric Use

Safety and effectiveness in pediatric patients under 12 years of age have not been established.

Geriatric Use

Clinical studies of AZELEX® cream did not include sufficient numbers of subjects aged 65 and over to determine whether they respond differently from younger subjects.

ADVERSE REACTIONS

During U.S. clinical trials with AZELEX® cream, adverse reactions were generally mild and transient in nature. The most common adverse reactions occurring in approximately 1-5% of patients were pruritus, burning, stinging and tingling. Other adverse reactions such as erythema, dryness, rash, peeling, irritation, dermatitis, and contact dermatitis were reported in less than 1% of subjects. There is the potential for experiencing allergic reactions with use of AZELEX® cream.

In patients using azelaic acid formulations, the following additional adverse experiences have been reported rarely: worsening of asthma, vitiligo depigmentation, small depigmented spots, hypertrichosis, reddening (signs of keratosis pilaris), and exacerbation of recurrent herpes labialis.

DOSAGE AND ADMINISTRATION

After the skin is thoroughly washed and patted dry, a thin film of AZELEX® cream should be gently but thoroughly massaged into the affected areas twice daily, in the morning and evening. The hands should be washed following application. The duration of use of AZELEX® cream can vary from person to person and depends on the severity of the acne. Improvement of the condition occurs in the majority of patients with inflammatory lesions within four weeks.

HOW SUPPLIED

AZELEX® cream is supplied in a closed orifice tube with a white, spiked screwcap in the following sizes:

30 g - NDC 16110-869-30
50 g - NDC 16110-869-50

Storage: Protect from freezing. Store product on its side. Store at 15°-30° C (59°-86° F).

Revised: 02/2024

Distributed by Almirall, LLC, Malvern, PA 19355, U.S.A.
© 2019 Almirall. All right reserved.
® marks owned by Almirall, LLC.

Made in Italy by LEO Pharma Manufacturing Italy S.r.l., Segrate (Milan), Italy